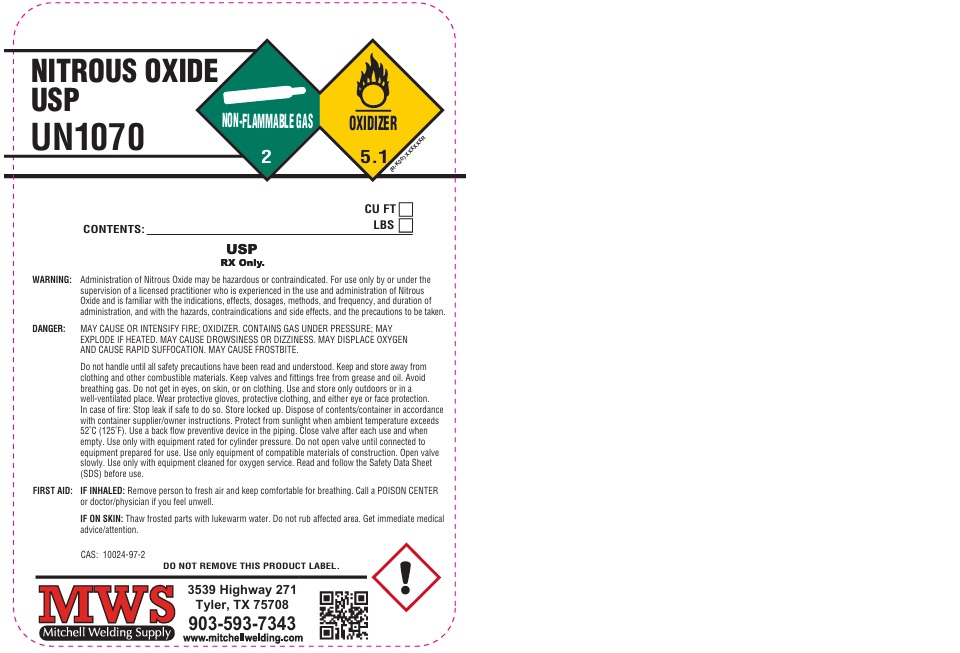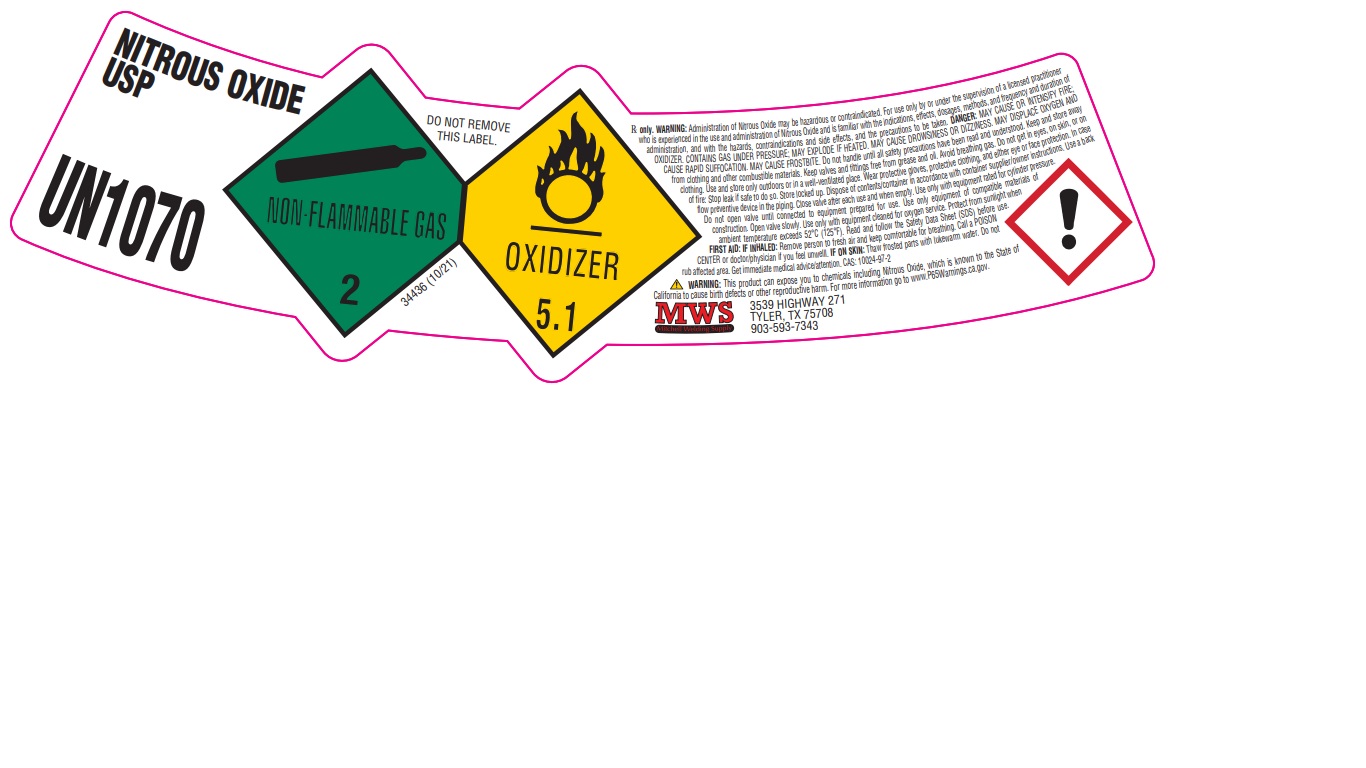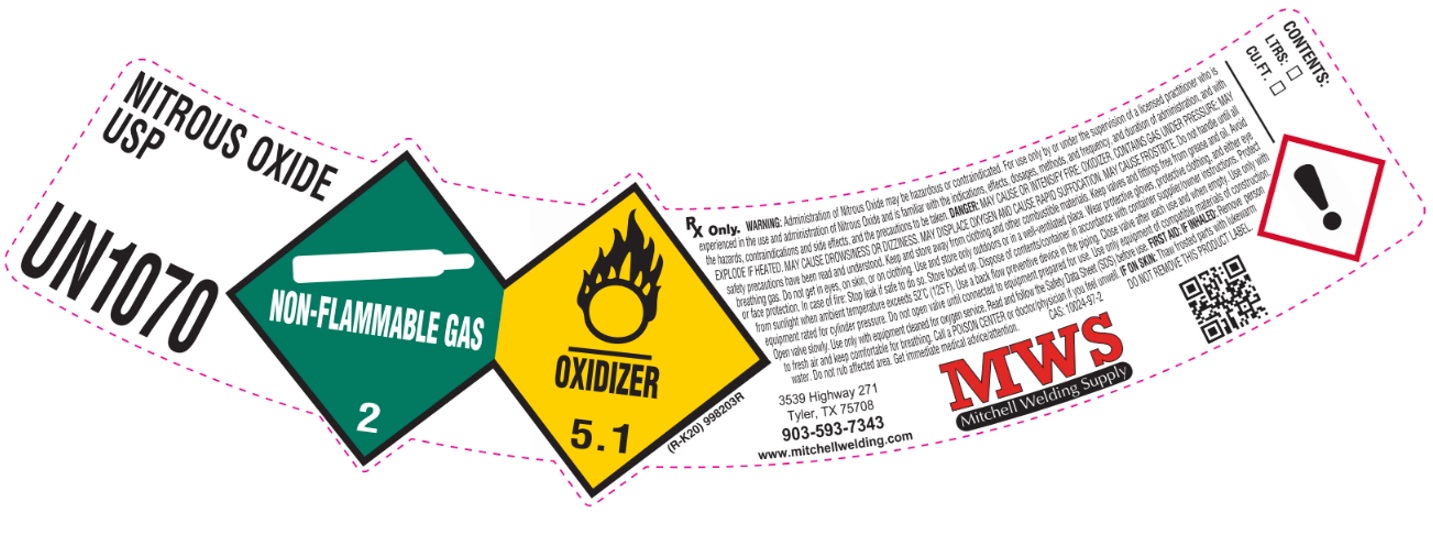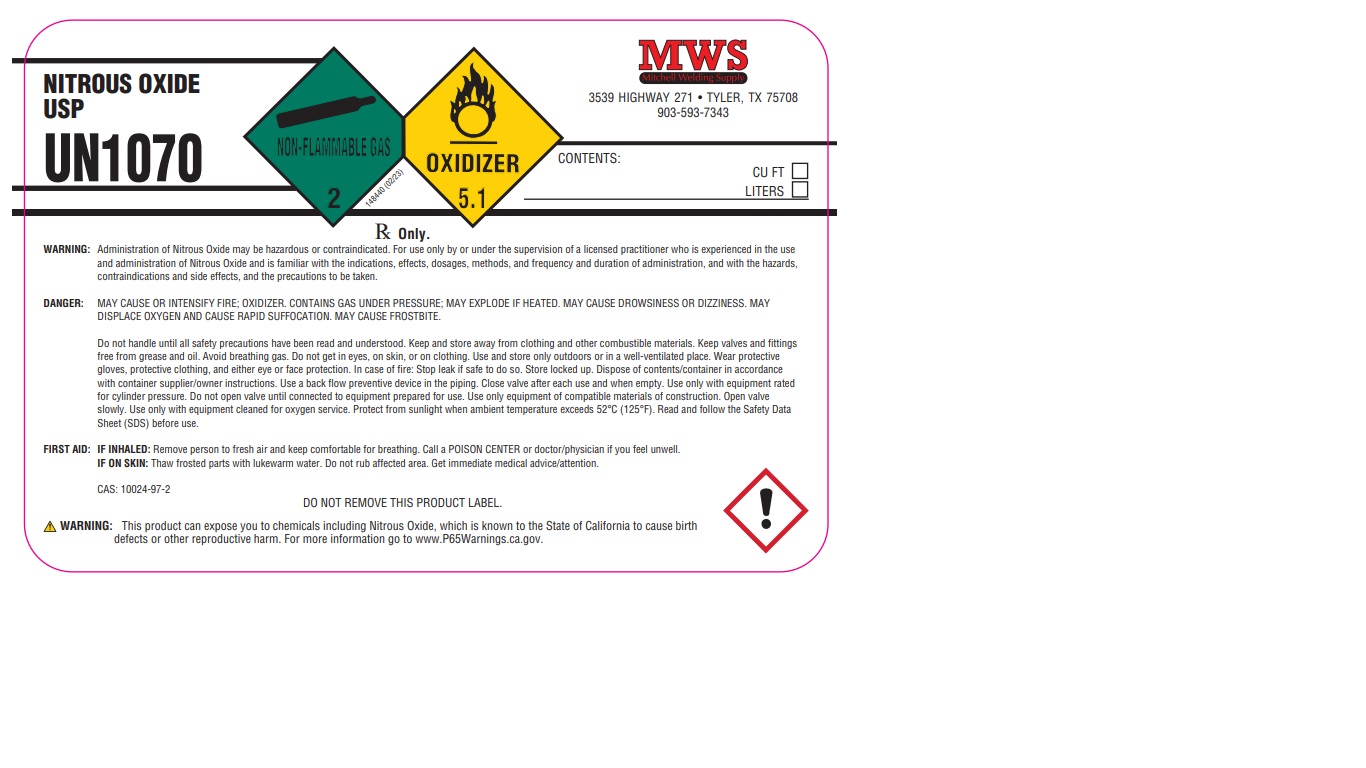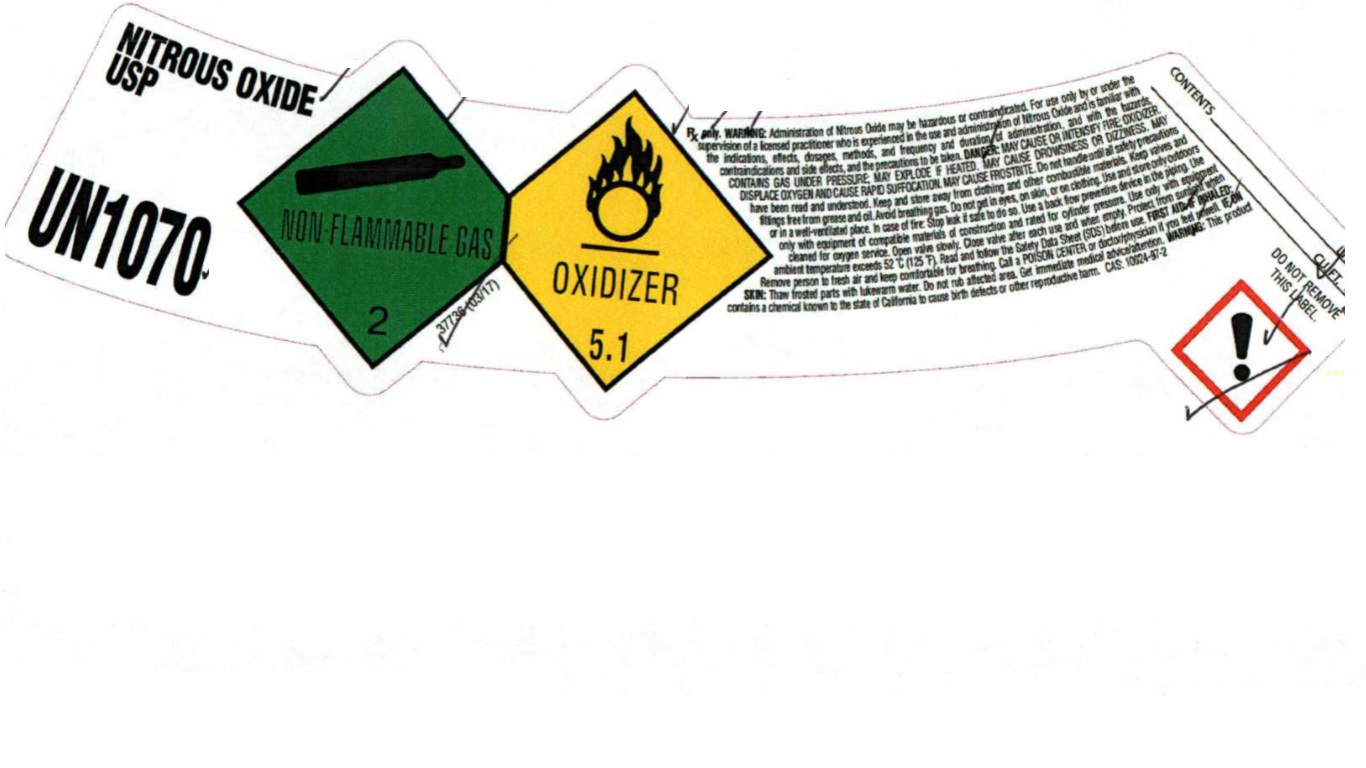 DRUG LABEL: Nitrous Oxide
NDC: 72276-002 | Form: GAS
Manufacturer: MITCHELL WELDING SUPPLY
Category: prescription | Type: HUMAN PRESCRIPTION DRUG LABEL
Date: 20251120

ACTIVE INGREDIENTS: NITROUS OXIDE 990 mL/1 L

Nitrous Oxide

PACKAGE LABEL

NITROUS OXIDE USP

UN1070

Rx only. WARNING: Administration of Nitrous Oxide may be hazardous or contraindicated. For use only by or under the supervision of a licensed practitioner who is experienced in the use and administration of Nitrous Oxide and is familiar with the indications, effects, dosages, methods, and frequency and duration of administration, and with the hazards, contraindications and side effects, and the precautions to be taken. DANGER: MAY CAUSE DROWSINESS OR DIZZINESS. MAY DISPLACE OXYGEN AND CAUSE RAPID SUFFOCATION. MAY CAUSE FROSTBITE. Do not handle until all safety precautions have been read and understood. Keep and store away from clothing and other combustible materials. Keep valves and fittings free from grease and oil. Avoid breathing gas. Do not get in eyes, on skin, or on clothing. Use and store only outdoors or in a well-ventilated place. In case of fire: Stop leak if safe to do so. Use a back flow preventive device in the piping. Use only with equipment of compatible materials of construction and rated for cylinder pressure. Use only with equipment cleaned for oxygen service. Open valve slowly. Close valve after each use and when empty. Protect from sunlight when ambient temperature exceeds 52C (125F). Read and follow the Safety Data Sheet (SDS) before use. FIRST AID: INHALED: Remove person to fresh air and keep comfortable for breathing. Call a POISON CENTER or doctor/physician if you feel unwell. IF ON SKIN: Thaw frosted parts with lukewarm water. Do not rub affected area. Get immediate medical advice/attention. WARNING: This product contains a chemical known to the state of California to cause birth defects or other reproductive harm. CAS: 10024-97-2

PACKAGE LABEL

NITROUS OXIDE USP

UN1070

DO NOT REMOVE THIS LABEL.

Rx only. WARNING: Administration of Nitrous Oxide may be hazardous or contraindicated. For use only by or under the supervision of a licensed practitioner who is experienced in the use and administration of Nitrous Oxide and is familiar with the indications, effects, dosages, methods, and frequency and duration of administration, and with the hazards, contraindications and side effects, and the precautions to be taken. DANGER: MAY CAUSE OR INTENSIFY FIRE; OXIDIZER. CONTAINS GAS UNDER PRESSURE; MAY EXPLODE IF HEATED. MAY CAUSE DROWSINESS OR DIZZINESS. MAY DISPLACE OXYGEN AND CAUSE RAPDI SUFFOCATION. MAY CAUSE FROSTBITE. Do not handle until all safety precautions have been read and understood. Keep and store away from clothing and other combustible materials. Keep valves and fittings free from grease and oil. Avoid breathing gas. Do not get in eyes, on skin, or on clothing. Use and store only outdoors or in a well-ventilated place. Wear protective gloves, protective clothing, and either eye or face protection. In vase of fire: Stop leak if safe to do so. Store locked up. Dispose of contents/container in accordance with container supplier/owner instructions. Use a back flow preventive device in the piping. Close valve after each use and when empty. Use only with equipment rated for cylinder pressure. Do not open valve until connected to equipment prepared for use. Use only equipment of compatible materials of construction. Open valve slowly. Use only with equipment cleaned for oxygen service. Protect from sunlight when ambient temperature exceeds 52 C (125 F). Read and follow the Safety Data Sheet (SDS) before use. FIRST AID: IF INHALED: Remove person to fresh air and keep comfortable for breathing. Call a POISON CENTER or doctor/physician if you feel unwell. IF ON SKIN: Thaw frosted parts with lukewarm water. Do not rub affected area. Get immediate medical advice/attention. CAS: 10024-97-2

WARNING: This product can expose you to chemical including Nitrous Oxide, which is known to the State of California to cause birth defects or other reproductive harm. For more information go to www.p65Warnings.ca.gov

MWS

Mitchell Welding Supply

3539 HIGHWAY 271

TYLER, TX 75708

903-593-7343

PACKAGE LABEL

NITROUS OXIDE USP

UN1070

MWS

Mitchell Welding Supply

3539 HIGHWAY 271. TYLER, TX 75708

903-593-7343

CONTENTS: CU FT LITERS

Rx Only.

WARNING: Administration of Nitrous Oxide may be hazardous or contraindicated. For use only by or under the supervision of a licensed practitioner who is experienced in the use and administration of Nitrous Oxide and is familiar with the indications, effects, dosages, methods, and frequency and duration of administration, and with the hazards, contraindications and side effects, and the precautions to be taken.

DANGER: MAY CAUSE OR INTENSIFY FIRE; OXIDIZER. CONTAINS GAS UNDER PRESSURE; MAY EXPLODE IF HEATED. MAY CAUSE DROWSINESS OR DIZZINESS. MAY DISPLACE OXYGEN AND CAUSE RAPID SUFFOCATION. MAY CAUSE FROSTBITE.

Do not handle until all safety precautions have been read and understood. Keep and store away from clothing and other combustible materials. Keep valves and fittings free from grease and oil. Avoid breathing gas. Do not get in eyes, on skin, or on clothing. Use and store only outdoors or in a well-ventilated place. Wear protective gloves, protective clothing, and either eye or face protection. In case of fire: Stop leak if safe to do so. Store locked up. Dispose of contents/container in accordance with container supplier/owner instructions. Use a back flow preventive device in the piping. Close valve after each use and when empty. Use only with equipment rated for cylinder pressure. Do not open valve until connected to equipment prepared for use. Use only equipment of compatible materials of construction. Open valve slowly. Use only with equipment cleaned for oxygen service. Protect from sunlight when ambient temperature exceeds 52 C (125 F). Read and follow the Safety Data Sheet (SDS) before use.

FIRST AID: IF INHALED: Remove person to fresh air and keep comfortable for breathing. Call a POISON CENTER or doctor/physician if you fell unwell.

IF ON SKIN: Thaw frosted parts with lukewarm water. Do not rub affected area. Get immediate medical advice/attention.

CAS: 10024-97-2 DO NOT REMOVE THIS PRODUCT LABEL.

WARNING: This product can expose you to chemicals including Nitrous Oxide, which is know to the State of California to cause birth defects or other reproductive harm. For more information go to www.P65Warnings.ca.gov.

PACKAGE LABEL

NITROUS OXIDE USP

UN1070

CONTENTS: CU FT LBS

USP

RX Only.

WARNING: Administration of Nitrous Oxide may be hazardous or contraindicated. For use only by or under the supervision of a licensed practitioner who is experienced in the use and administration of Nitrous Oxide and is familiar with the indications, effects, dosages, methods, and frequency, and duration of administration, and with the hazards, contraindications and side effects, and the precautions to be taken.

DANGER: MAY CAUSE OR INTENSIFY FIRE; OXIDIZER. CONTAINS GAS UNDER PRESSURE; MAY EXPLODE IF HEATED. MAY CAUSE DROWSINESS OR DIZZINESS. MAY DISPLACE OXYGEN AND CAUSE RAPID SUFFOCATION. MAY CAUSE FROSTBITE.

Do not handle until all safety precautions have been read and understood. Keep and store away from clothing and other combustible materials. Keep valves and fittings free from grease and oil. Avoid breathing gas. Do not get in eyes, on skin, or on clothing. Use and store only outdoors or in a well-ventilated place. Wear protective gloves, protective clothing, and either eye or face protection. In case of fire: Stop leak if safe to do so. Store locked up. Dispose of contents/container in accordance with container supplier/owner instructions. Protect from sunlight when ambient temperature exceeds 52 C (125 F). Use a back flow preventive device in the piping. Close valve after each use and when empty. Use only with equipment rated for cylinder pressure. Do not open valve until connected to equipment prepared for use. Use only equipment of compatible materials of construction. Open valve slowly. Use only with equipment cleaned for oxygen service. Read and follow the Safety Data Sheet (SDS) before use.

FIRST AID: IF INHALED: Remove person to fresh air and keep comfortable for breathing. Call a POISON CENTER or doctor/physician if you feel unwell.

IF ON SKIN: Thaw frosted parts with lukewarm water. Do not rub affected area. Get immediate medical advice/attention.

DO NOT REMOVE THIS PRODUCT LABEL.

MWS

Mitchell Welding Supply

3539 Highway 271

Tyler, TX 75708

903-593-7343

www.mitchellwelding.com

PACKAGE LABEL

NITROUS OXIDE USP

UN1070

RX Only. WARNING: Administration of Nitrous Oxide may be hazardous or contraindicated. For use only by or under the supervision of a licensed practitioner who is experienced in the use and administration of Nitrous Oxide and is familiar with the indications, effects, dosages, methods, and frequency, and duration of administration, and with the hazards, contraindications and side effects, and the precautions to be taken. DANGER: MAY CAUSE OR INTENSIFY FIRE; OXIDIZER. CONTAINS GAS UNDER PRESSURE; MAY EXPLODE IF HEATED. MAY CAUSE DROWSINESS OR DIZZINESS. MAY DISPLACE OXYGEN AND CAUSE RAPID SUFFOCATION. MAY CAUSE FROSTBITE. Do not handle until all safety precautions have been read and understood. Keep and store away from clothing and other combustible materials. Keep valves and fittings free from grease and oil. Avoid breathing gas. Do not get in eyes, on skin, or on clothing. Use and store only outdoors or in a well-ventilated place. Wear protective gloves, protective clothing, and either eye or face protection. In case of fire: Stop leak if safe to do so. Store locked up. Dispose of contents/containers in accordance with container supplier/owner instructions. Protect from sunlight when ambient temperature exceeds 52 C (125 F). Use a back flow preventive device in the piping. Close valve after each use and when empty. Use only with equipment rated for cylinder pressure. Do not open valve until connected to equipment prepared for use. Use only equipment of compatible materials of construction. Open valve slowly. Use only with equipment cleaned for oxygen service. Read and follow the Safety Data Sheet (SDS) before use. IFRST AID: IF INHALED: Remove person to fresh air and keep comfortable for breathing. Call a POSION CENTER or doctor/physician if you feel unwell. IF ON SKIN: Thaw frosted parts with lukewarm water. Do not rub affected area. Get immediate medical advice/attention. CAS: 10024-97-2 DO NOT REMOVE THIS PRODUCT LABEL.

MWS

Mitchell Welding Supply

3539 Highway 271

Tyler, TX 75708

903-593-7343

www.mitchellwelding.com

CONTENTS: LTRS: CU.FT.